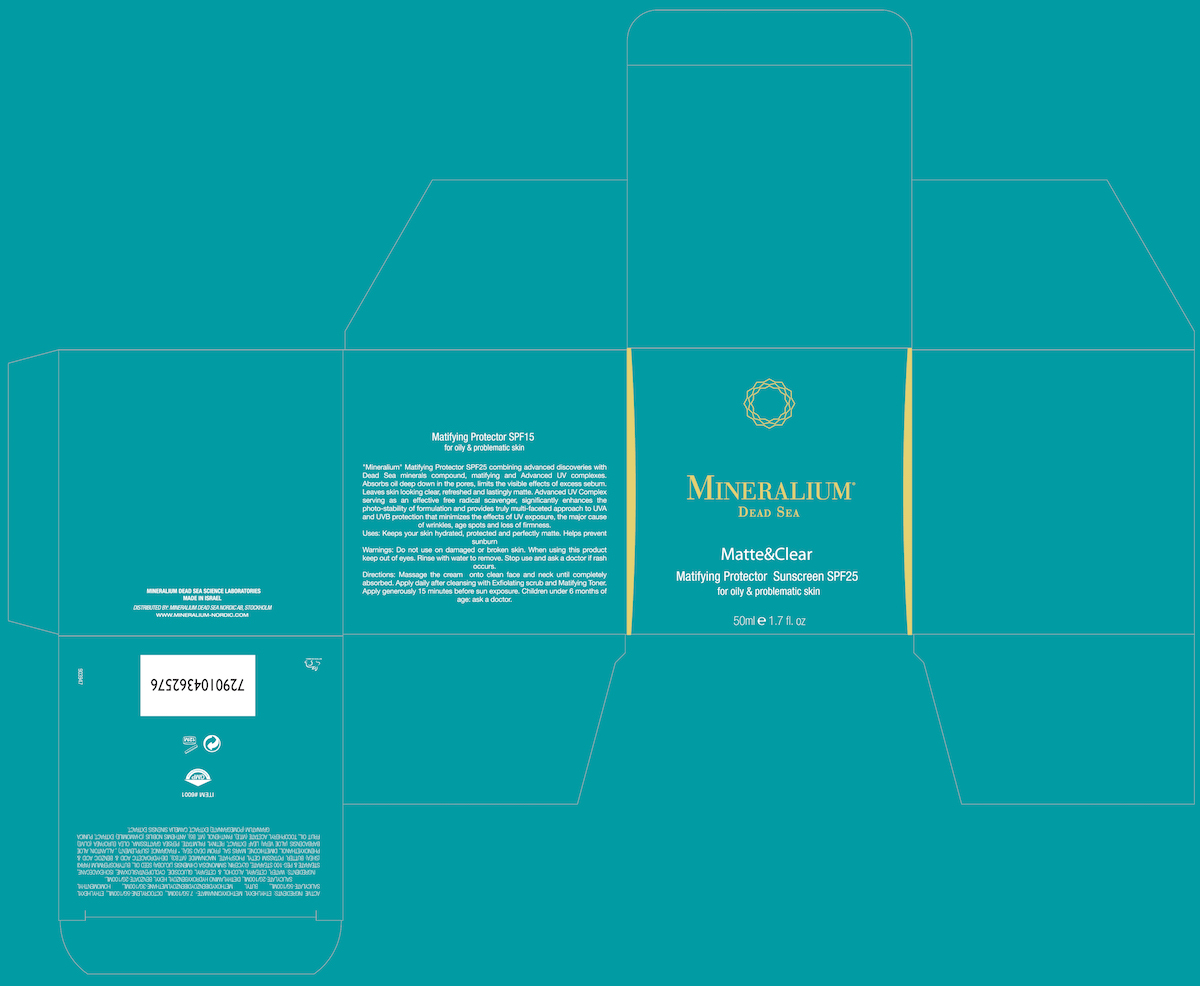 DRUG LABEL: Matte and Clear Matifying Protector SPF 25
NDC: 69435-1610 | Form: CREAM
Manufacturer: Peer Pharm Ltd.
Category: otc | Type: HUMAN OTC DRUG LABEL
Date: 20160325

ACTIVE INGREDIENTS: OCTOCRYLENE 5 g/100 mL; OCTISALATE 5 g/100 mL; AVOBENZONE 3 g/100 mL; HOMOSALATE 2 g/100 mL; OCTINOXATE 7.5 g/100 mL
INACTIVE INGREDIENTS: CETOSTEARYL ALCOHOL; CETEARYL GLUCOSIDE; CYCLOMETHICONE 5; ISOHEXADECANE; GLYCERIN; SIMMONDSIA CHINENSIS SEED; SHEA BUTTER; POTASSIUM CETYL PHOSPHATE; NIACINAMIDE; DIMETHICONE; SEA SALT; ALOE VERA LEAF; VITAMIN A PALMITATE; .ALPHA.-TOCOPHEROL ACETATE; PANTHENOL; CHAMOMILE FLOWER OIL; POMEGRANATE SEED OIL; CAMELINA SATIVA WHOLE; WATER

Matte & Clear Matifying Protector SPF 25

PACKAGE LABEL

ACTIVE INGREDIENT

Octinoxate 7.5%

Octocrylene 5%

Octisalate 5%

Avobenzone 3%

Homosalate 2%

Keep out of reach of children.

PURPOSE

Provides SPF 25 protection

INDICATIONS AND USAGE

To Use: Smooth onto face.
For Sunscreen Use: Apply liberally 15 minutes before sun exposure. Reapply at least every 2 hours.
Sun Protection Measures: Spending time in the sun increases your risk of skin cancer and early skin aging. To decrease this risk, regularly use a sunscreen with a broad spectrum SPF of 15 or higher and other sun protection measures including: Limit time in the sun, especially from 10 a.m. - 2 p.m. Wear long-sleeve shirts, pants, hats, and sunglasses.

DOSAGE AND ADMINISTRATION

Smooth on to face.

INACTIVE INGREDIENT

Water, Cetearyl Alcohol & Cetearyl Glucoside, Cyclopentasiloxane, Isohexadecane, Stearate & Peg-100 stearate, Glycerin, Simmondsia Chimensis (Jojoba) seed oil, Butyrospermum Parkii (shea) Butter, Potassim Cetyl Phosphate, Niacinamide (Vit.B3), Dehydroacetic Acid & Benzoic Acid & Phenoxyethanol, Dimethicone, Maris Sal (from dead sea), * Fragrance (supplement) , Allantoin, Aloe Barbadensis (Aloe Vera) Leaf extract, Retinyl Palmitate, Persea Grattissima, Olea Europaea (Olive) fruit oil, Tocopheryl Acetate (vit.E), Panthenol (vit. B5), Anthemis Nobilis (Chamomile) extract, Punica Granatum (Pomegranate) extract, Camelia Sinensis extract.